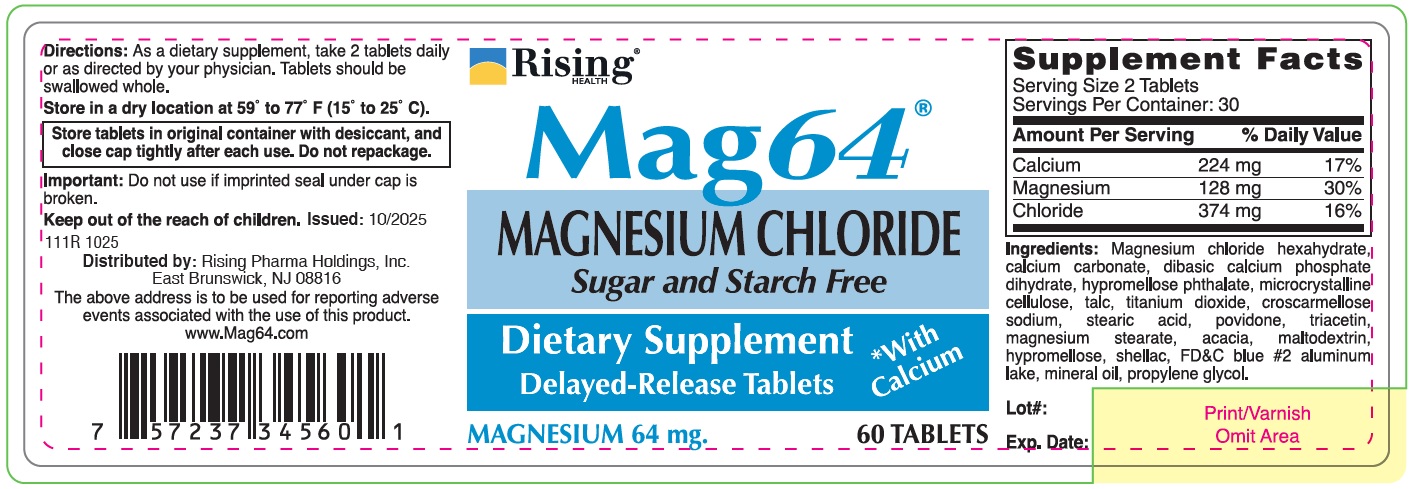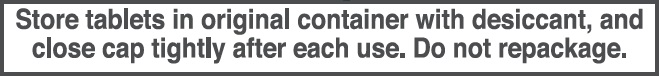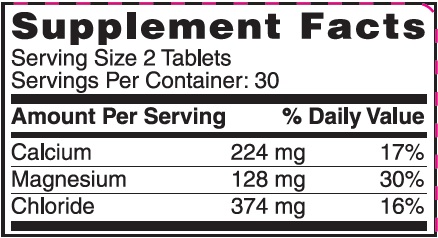 DRUG LABEL: Mag64
NDC: 57237-345 | Form: TABLET, DELAYED RELEASE
Manufacturer: Rising Pharma Holdings, Inc.
Category: other | Type: DIETARY SUPPLEMENT
Date: 20251210

ACTIVE INGREDIENTS: MAGNESIUM CHLORIDE 535 mg/1 1
INACTIVE INGREDIENTS: CALCIUM CARBONATE; DIBASIC CALCIUM PHOSPHATE DIHYDRATE; HYPROMELLOSE PHTHALATE (24% PHTHALATE, 55 CST); MICROCRYSTALLINE CELLULOSE; TALC; TITANIUM DIOXIDE; CROSCARMELLOSE SODIUM; STEARIC ACID; POVIDONE; TRIACETIN; MAGNESIUM STEARATE; ACACIA; MALTODEXTRIN; HYPROMELLOSE, UNSPECIFIED; SHELLAC; FD&C BLUE NO. 2 ALUMINUM LAKE; MINERAL OIL; PROPYLENE GLYCOL

Mag64®Magnesium Chloride, Delayed-Release Tablets, 60 Tablets (Dietary Supplement)

HEALTH CLAIM

Ingredients: Magnesium chloride hexahydrate, calcium carbonate, dibasic calcium phosphate dihydrate, hypromellose phthalate, microcrystalline cellulose, talc, titanium dioxide, croscarmellose sodium, stearic acid, povidone, triacetin, magnesium stearate, acacia, maltodextrin, hypromellose, shellac, FD&C blue #2 aluminum lake, mineral oil, propylene glycol.

DOSAGE AND ADMINISTRATION

Directions: As a dietary supplement, take 2 tablets daily or as directed by your physician. Tablets should be swallowed whole.

Store in a dry location at 59° to 77° F (15° to 25° C).

WARNINGS

lmportant: Do not use if imprinted seal under cap is broken.

SAFE HANDLING WARNING

Keep out of the reach of children. Issued: 10/2025

111R 1025

Distributed by: Rising Pharma Holdings, Inc.
East Brunswick, NJ 08816

The above address is to be used for reporting adverse events associated with the use of this product. www.Mag64.com

PACKAGE LABEL.PRINCIPAL DISPLAY PANEL

Mag64®

Magnesium Chloride

Sugar and Starch Free Delayed-Release Tablets, with Calcium

MAGNESIUM 64 mg

60 Tablets

DIETARY SUPPLEMENT

Bottle Label (57237-345-60)